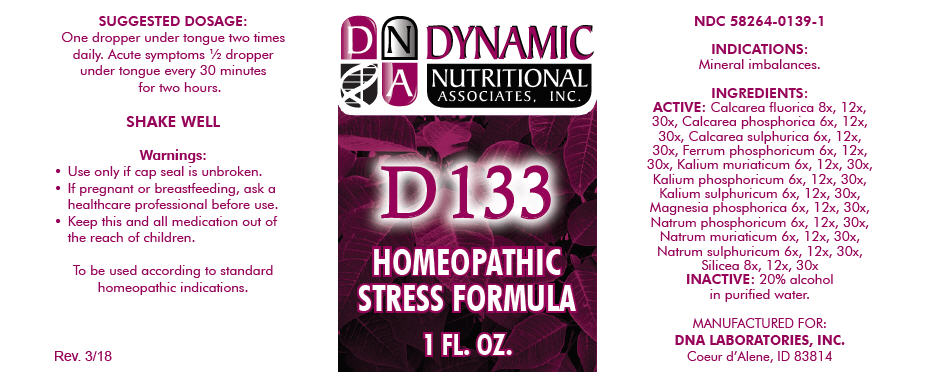 DRUG LABEL: D-133
NDC: 58264-0139 | Form: SOLUTION
Manufacturer: DNA Labs, Inc.
Category: homeopathic | Type: HUMAN OTC DRUG LABEL
Date: 20250113

ACTIVE INGREDIENTS: CALCIUM FLUORIDE 8 [hp_X]/1 mL; SILICON DIOXIDE 8 [hp_X]/1 mL; TRIBASIC CALCIUM PHOSPHATE 6 [hp_X]/1 mL; CALCIUM SULFATE ANHYDROUS 6 [hp_X]/1 mL; FERROSOFERRIC PHOSPHATE 6 [hp_X]/1 mL; POTASSIUM CHLORIDE 6 [hp_X]/1 mL; DIBASIC POTASSIUM PHOSPHATE 6 [hp_X]/1 mL; POTASSIUM SULFATE 6 [hp_X]/1 mL; MAGNESIUM PHOSPHATE, DIBASIC TRIHYDRATE 6 [hp_X]/1 mL; SODIUM PHOSPHATE, DIBASIC, HEPTAHYDRATE 6 [hp_X]/1 mL; SODIUM CHLORIDE 6 [hp_X]/1 mL; SODIUM SULFATE 6 [hp_X]/1 mL
INACTIVE INGREDIENTS: ALCOHOL; WATER

D-133

NDC 58264-0139-1

INDICATIONS

PURPOSE

Mineral imbalances.

INGREDIENTS

ACTIVE

Calcarea fluorica 8x, 12x, 30x, Calcarea phosphorica 6x, 12x, 30x, Calcarea sulphurica 6x, 12x, 30x, Ferrum phosphoricum 6x, 12x, 30x, Kalium muriaticum 6x, 12x, 30x, Kalium phosphoricum 6x, 12x, 30x, Kalium sulphuricum 6x, 12x, 30x, Magnesia phosphorica 6x, 12x, 30x, Natrum phosphoricum 6x, 12x, 30x, Natrum muriaticum 6x, 12x, 30x, Natrum sulphuricum 6x, 12x, 30x, Silicea 8x, 12x, 30x

INACTIVE

20% alcohol in purified water.

SUGGESTED DOSAGE

One dropper under tongue two times daily. Acute symptoms ½ dropper under tongue every 30 minutes for two hours.

STORAGE AND HANDLING

SHAKE WELL

Warnings

- Use only if cap seal is unbroken.

PREGNANCY OR BREAST FEEDING

- If pregnant or breastfeeding, ask a healthcare professional before use.

KEEP OUT OF REACH OF CHILDREN

- Keep this and all medication out of the reach of children.

To be used according to standard homeopathic indications.

PRINCIPAL DISPLAY PANEL - 1 FL. OZ. Bottle Label

DYNAMIC
NUTRITIONAL
ASSOCIATES, INC.

D 133

HOMEOPATHIC
STRESS FORMULA

1 FL. OZ.